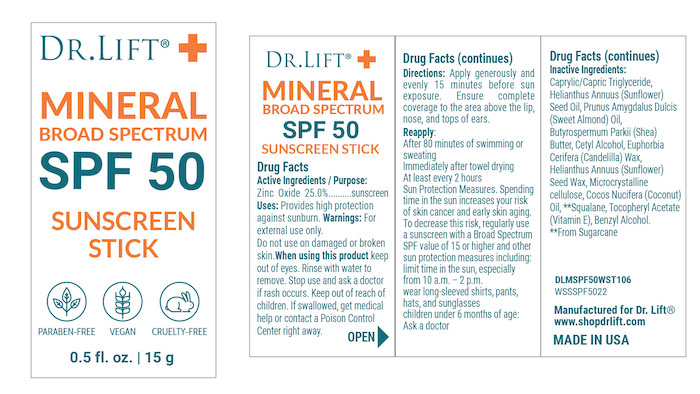 DRUG LABEL: Dr Lift SPF 50 Mineral Sunscreen Stick
NDC: 68062-8314 | Form: STICK
Manufacturer: Spa de Soleil
Category: otc | Type: HUMAN OTC DRUG LABEL
Date: 20251112

ACTIVE INGREDIENTS: ZINC OXIDE 3.75 g/15 g
INACTIVE INGREDIENTS: CAPRYLIC/CAPRIC TRIGLYCERIDE; HELIANTHUS ANNUUS SEED WAX; PRUNUS AMYGDALUS DULCIS (SWEET ALMOND) OIL; BUTYROSPERMUM PARKII (SHEA) BUTTER; CETYL ALCOHOL; EUPHORBIA CERIFERA (CANDELILLA) WAX; HELIANTHUS ANNUUS (SUNFLOWER) SEED OIL UNSAPONIFIABLES; MICROCRYSTALLINE CELLULOSE; COCOS NUCIFERA (COCONUT) OIL; SQUALANE; .ALPHA.-TOCOPHEROL ACETATE, D-; BENZYL ALCOHOL

Dr Lift SPF 50 Clear Stick

Active Ingredients

Zinc Oxide 25%

Purpose

Sunscreen

Warnings

For external use only. Do not use on damaged or broken skin.When using this product keep out of eyes. Rinse with water to remove. Stop use and ask a doctor if rash occurs. Keep out of reach of children. If swallowed, get medical help or contact a Poison Control Center right away.

Keep out of reach of children.

DOSAGE AND ADMINISTRATION

Directions: Apply generously and evenly 15 minutes before sun exposure. Ensure complete coverage to the area above the lip, nose, and tops of ears.

Uses
Provides high protection against sunburn.

Inactive Ingredients

Inactive Ingredients: Caprylic/Capric Triglyceride, Helianthus Annuus (Sunflower) Seed Oil, Prunus Amygdalus Dulcis (Sweet Almond) Oil, Butyrospermum Parkii (Shea) Butter, Cetyl Alcohol, Euphorbia Cerifera (Candelilla) Wax, Helianthus Annuus (Sunflower) Seed Wax, Microcrystalline cellulose, Cocos Nucifera (Coconut) Oil, **Squalane, Tocopheryl Acetate (Vitamin E), Benzyl Alcohol.